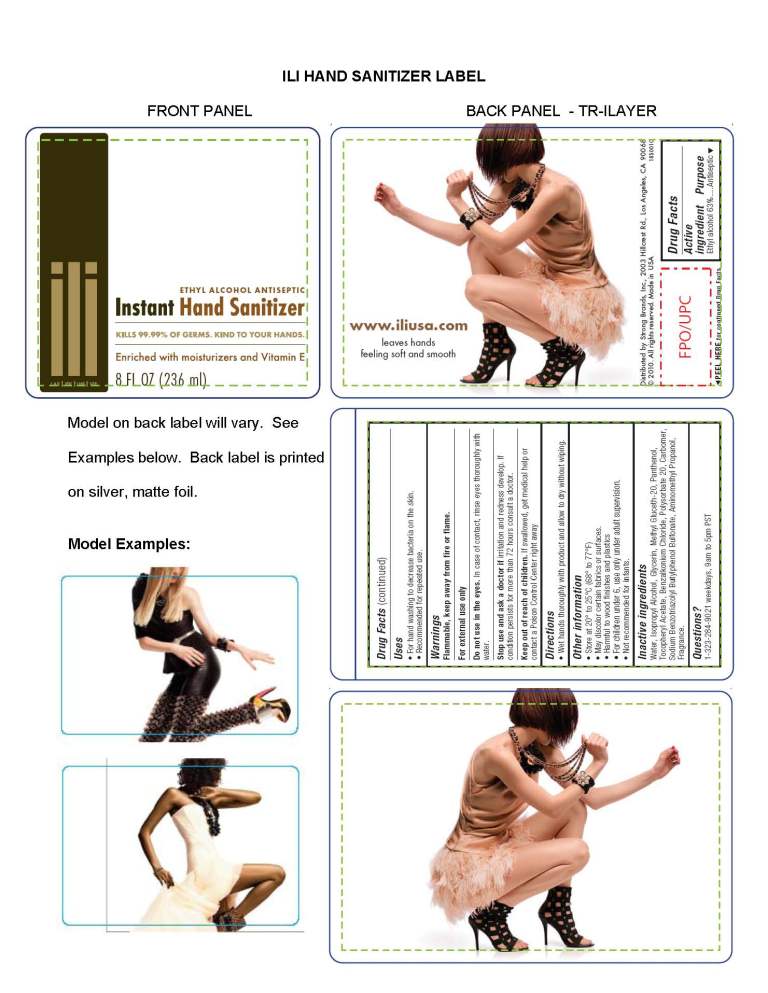 DRUG LABEL: Ili Hand Sanitizer
NDC: 50859-100 | Form: GEL
Manufacturer: Strong Brands, Inc.
Category: otc | Type: HUMAN OTC DRUG LABEL
Date: 20100630

ACTIVE INGREDIENTS: Alcohol 63 mL/100 mL

Drug Facts

Active Ingredient: Ethyl Alcohol 63%

Purpose: Antiseptic

INDICATIONS AND USAGE

Use: For hand washing to decrease bacteria on the skin. Recommended for repeated use.

WARNINGS

Warnings: Flammable, keep away from fire or flame. For external use only. Do not use in the eyes. In case of contact, rinse eyes thoroughly with water.

Stop use and ask a doctor if irritation and redness develop. If condition persists for more than 72 hours consult a doctor.

Keep out of reach of children. If swallowed, get medical help or contact a Poison Control Center right away.

DOSAGE AND ADMINISTRATION

Directions: Wet hands thoroughly with product and allow to dry without wiping.

QUESTIONS

Questions? 1-323-284-9021 weekdays, 9am to 5pm PST

ili Hand Sanitizer 8 fl oz

MM1:8floz_ILI_Hand_Sanitizer_Label rev 3_Page_1.jpg

INACTIVE INGREDIENT

water, isopropyl alcohol, glycerin, methyl gluceth-20, panthenol, tocopheryl acetate, benzalkonium chloride, polysorbate 20, carbomer, sodium benzotriazolyl butylphenol sulfonate, aminomethyl propanol, fragrance